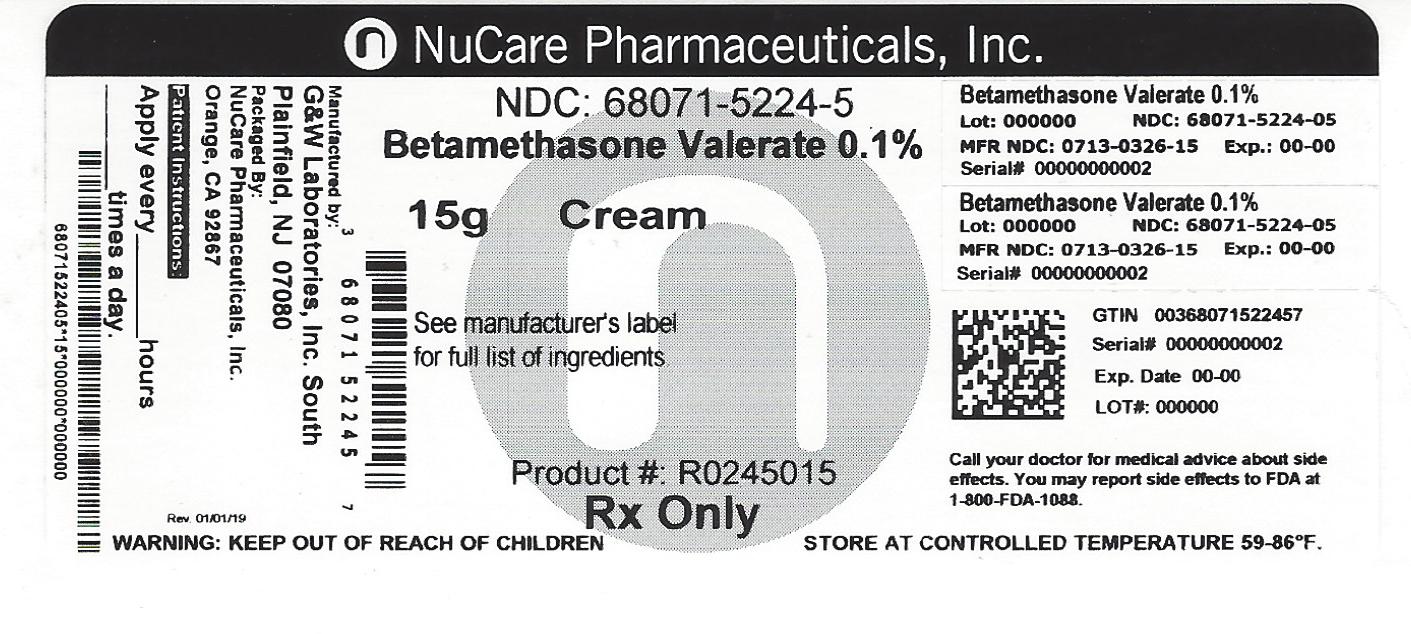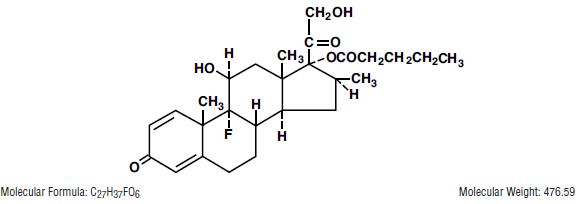 DRUG LABEL: Betamethasone Valerate
NDC: 68071-5224 | Form: CREAM
Manufacturer: NuCare Pharmaceuticals,Inc.
Category: prescription | Type: HUMAN PRESCRIPTION DRUG LABEL
Date: 20240620

ACTIVE INGREDIENTS: BETAMETHASONE VALERATE 1.2 mg/1 g
INACTIVE INGREDIENTS: WATER; MINERAL OIL; SODIUM PHOSPHATE, MONOBASIC; PETROLATUM; POLYETHYLENE GLYCOL 1000; CETEARETH-15; STEARYL ALCOHOL; CETYL ALCOHOL; PROPYLENE GLYCOL; PHOSPHORIC ACID; CHLOROCRESOL

BETAMETHASONE VALERATE CREAM USP, 0.1%
BETAMETHASONE VALERATE OINTMENT USP, 0.1%
(Potency expressed as betamethasone)
Rx only
FOR DERMATOLOGIC USE ONLY.
NOT FOR OPHTHALMIC USE.

DESCRIPTION

Betamethasone Valerate Cream and Ointment contain betamethasone valerate USP, a synthetic adrenocorticosteroid for dermatologic use. Betamethasone, an analog of prednisolone, has a high degree of glucocorticoid activity and a slight degree of mineralocorticoid activity.
Betamethasone valerate is a white to practically white odorless crystalline powder practically insoluble in water, freely soluble in acetone and chloroform, soluble in alcohol, and slightly soluble in benzene and ether. Chemically, it is 9-fluoro-11β,17,21-trihydroxy-16β-methylpregna-1,4-diene-3,20-dione 17-valerate. The structural formula is:
Each gram of the 0.1% Cream contains 1.2 mg betamethasone valerate (equivalent to 1 mg betamethasone) in a soft, white, hydrophilic cream of purified water, mineral oil, sodium phosphate monobasic (monohydrate), white petrolatum, polyethylene glycol 1000, ceteareth-15, stearyl alcohol, cetyl alcohol, propylene glycol, phosphoric acid (to adjust pH, if required); chlorocresol is present as a preservative.
Each gram of the 0.1% Ointment contains 1.2 mg betamethasone valerate (equivalent to 1 mg betamethasone) in an ointment base of white petrolatum, mineral oil, and hydrogenated lanolin.

CLINICAL PHARMACOLOGY

Topical corticosteroids share anti-inflammatory, antipruritic and vasoconstrictive actions.
The mechanism of anti-inflammatory activity of the topical corticosteroids is unclear. Various laboratory methods, including vasoconstrictor assays, are used to compare and predict potencies and/or clinical efficacies of the topical corticosteroids. There is some evidence to suggest that a recognizable correlation exists between vasoconstrictor potency and therapeutic efficacy in man.

Pharmacokinetics

The extent of percutaneous absorption of topical corticosteroids is determined by many factors including the vehicle, the integrity of the epidermal barrier, and the use of occlusive dressings.
Topical corticosteroids can be absorbed from normal intact skin. Inflammation and/or other disease processes in the skin increase percutaneous absorption. Occlusive dressings substantially increase the percutaneous absorption of topical corticosteroids. Thus, occlusive dressings may be a valuable therapeutic adjunct for treatment of resistant dermatoses.
Once absorbed through the skin, topical corticosteroids are handled through pharmacokinetic pathways similar to systemically administered corticosteroids. Corticosteroids are bound to plasma proteins in varying degrees. Corticosteroids are metabolized primarily in the liver and are then excreted by the kidneys. Some of the topical corticosteroids and their metabolites are also excreted into the bile.

INDICATIONS AND USAGE

Topical corticosteroids are indicated for the relief of the inflammatory and pruritic manifestations of corticosteroid-responsive dermatoses.

CONTRAINDICATIONS

Topical corticosteroids are contraindicated in those patients with a history of hypersensitivity to any of the components of the preparation.

General

Systemic absorption of topical corticosteroids has produced reversible hypothalamic-pituitary-adrenal (HPA) axis suppression, manifestations of Cushing's syndrome, hyperglycemia, and glucosuria in some patients.
Conditions which augment systemic absorption include the application of the more potent steroids, use over large surface areas, prolonged use, and the addition of occlusive dressings.
Therefore, patients receiving a large dose of a potent topical steroid applied to a large surface area should be evaluated periodically for evidence of HPA axis suppression by using the urinary free cortisol and ACTH stimulation tests. If HPA axis suppression is noted, an attempt should be made to withdraw the drug, to reduce the frequency of application, or substitute to a less potent steroid.
Recovery of HPA axis function is generally prompt and complete upon discontinuation of the drug. Infrequently, signs and symptoms of steroid withdrawal may occur, requiring supplemental systemic corticosteroids.
Pediatric patients may absorb proportionally larger amounts of topical corticosteroids and thus be more susceptible to systemic toxicity (See PRECAUTIONS—Pediatric Use).
If irritation develops, topical corticosteroids should be discontinued and appropriate therapy instituted.
In the presence of dermatological infections, the use of an appropriate antifungal or antibacterial agent should be instituted. If a favorable response does not occur promptly, the corticosteroid should be discontinued until the infection has been adequately controlled.

Information for Patients

Patients using topical corticosteroids should receive the following information and instructions:
1. This medication is to be used as directed by the physician.. It is for external use only. Avoid contact with the eyes.
2. Patients should be advised not to use this medication for any disorder other than that for which it was prescribed.
3. The treated skin area should not be bandaged or otherwise covered or wrapped as to be occlusive unless directed by the physician.
4. Patients should report any signs of local adverse reactions especially under occlusive dressing.
5. Parents of pediatric patients should be advised not to use tight-fitting diapers or plastic pants on a child being treated in the diaper area, as these garments may constitute occlusive dressings.

Laboratory tests

The following tests may be helpful in evaluating the HPA axis suppression:
Urinary free cortisol test
ACTH stimulation test

Carcinogenesis, Mutagenesis and Impairment of Fertility

Long-term animal studies have not been performed to evaluate the carcinogenic potential or the effect on fertility of topical corticosteroids.
Studies to determine mutagenicity with prednisolone and hydrocortisone have revealed negative results.

Pregnancy

Teratogenic Effects — Pregnancy Category C
Corticosteroids are generally teratogenic in laboratory animals when administered systemically at relatively low dosage levels. The more potent corticosteroids have been shown to be teratogenic after dermal application in laboratory animals. There are no adequate and well-controlled studies in pregnant women on teratogenic effects from topically applied corticosteroids. Therefore, topical corticosteroids should be used during pregnancy only if the potential benefit justifies the potential risk to the fetus. Drugs of this class should not be used extensively on pregnant patients, in large amounts, or for prolonged periods of time.

Nursing Mothers

It is not known whether topical administration of corticosteroids could result in sufficient systemic absorption to produce detectable quantities in breast milk. Systemically administered corticosteroids are secreted into breast milk in quantities not likely to have a deleterious effect on the infant. Nevertheless, caution should be exercised when topical corticosteroids are administered to a nursing woman.

Pediatric Use

Pediatric patients may demonstrate greater susceptibility to topical corticosteroid-induced HPA axis suppression and Cushing's syndrome than mature patients because of a larger skin surface area to body weight ratio.
Hypothalamic-pituitary-adrenal (HPA) axis suppression, Cushing's syndrome, and intracranial hypertension have been reported in children receiving topical corticosteroids. Manifestations of adrenal suppression in children include linear growth retardation, delayed weight gain, low plasma cortisol levels, and absence of response to ACTH stimulation. Manifestations of intracranial hypertension include bulging fontanelles, headaches, and bilateral papilledema.
Administration of topical corticosteroids to pediatric patients should be limited to the least amount compatible with an effective therapeutic regimen. Chronic corticosteroid therapy may interfere with the growth and development of children.

ADVERSE REACTIONS

The following local adverse reactions are reported infrequently with topical corticosteroids, but may occur more frequently with the use of occlusive dressings. These reactions are listed in an approximate decreasing order of occurrence: burning, itching, irritation, dryness, folliculitis, hypertrichosis, acneiform eruptions, hypopigmentation, perioral dermatitis, allergic contact dermatitis, maceration of the skin, secondary infection, skin atrophy, striae and miliaria.
To report SUSPECTED ADVERSE REACTIONS, contact G&W Laboratories, Inc. at 1-800-922-1038 or FDA at 1-800-FDA-1088 or www.fda.gov/medwatch.

OVERDOSAGE

Topically applied corticosteroids can be absorbed in sufficient amounts to produce systemic effects (See PRECAUTIONS).

DOSAGE AND ADMINISTRATION

Apply a thin film of Betamethasone Valerate Cream or Ointment to the affected skin areas one to three times a day. Dosage once or twice a day is often effective.

HOW SUPPLIED

Betamethasone Valerate Cream USP, 0.1% is supplied as follows:
NDC 68071-5224-5 BOX OF 15g
Store at room temperature 15°-30°C (59°-86°F) [see USP Controlled Room Temperature].
Manufactured by:
G&W Laboratories, Inc.
111 Coolidge Street
South Plainfield, NJ 07080
8-BETVGW1
Issued: 09/2015